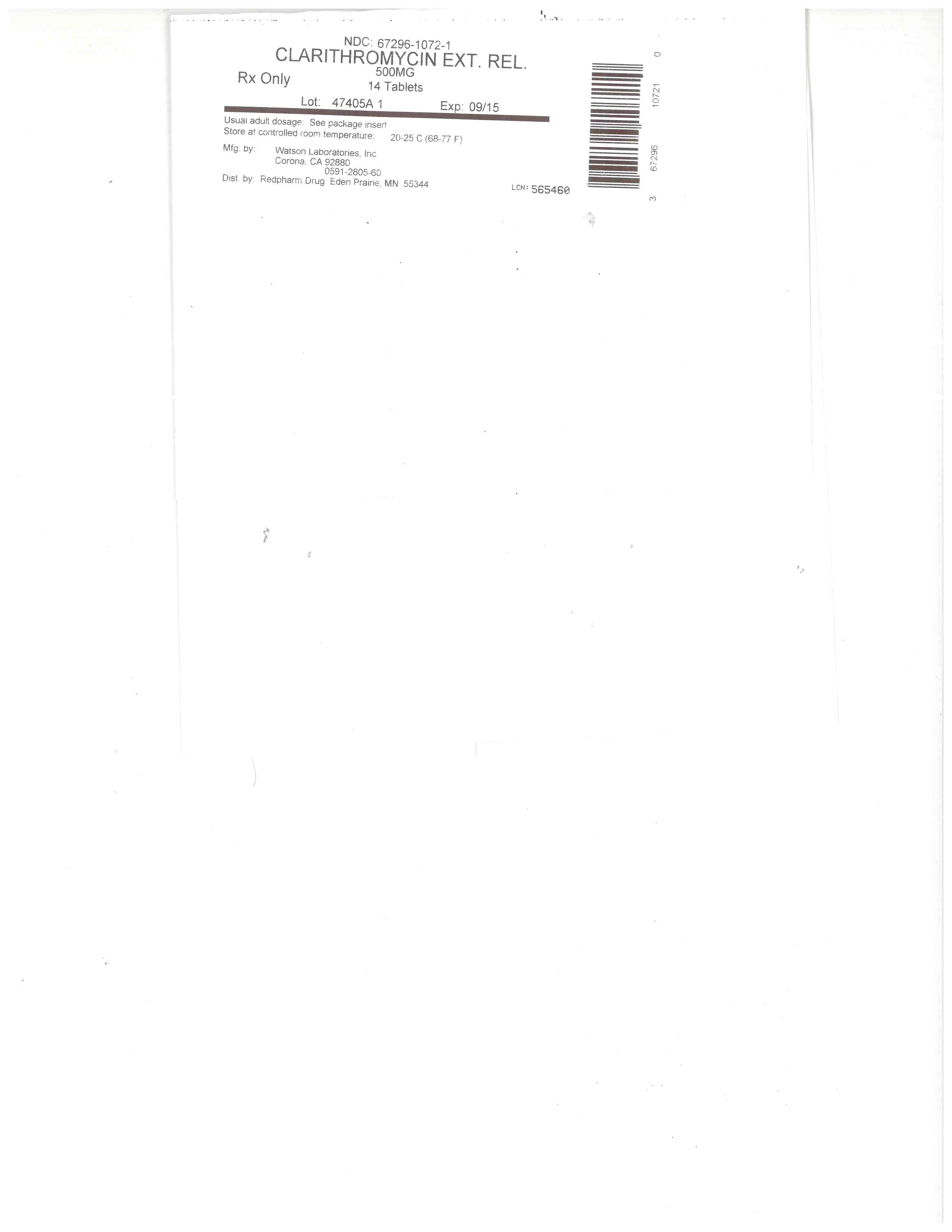 DRUG LABEL: clarithromycin
NDC: 67296-1072 | Form: TABLET, FILM COATED, EXTENDED RELEASE
Manufacturer: RedPharm Drug, Inc.
Category: prescription | Type: HUMAN PRESCRIPTION DRUG LABEL
Date: 20220120

ACTIVE INGREDIENTS: CLARITHROMYCIN 500 mg/1 1
INACTIVE INGREDIENTS: SUCROSE; GLYCERYL MONOSTEARATE; SODIUM PHOSPHATE, MONOBASIC, ANHYDROUS; D&C YELLOW NO. 10; POLYETHYLENE GLYCOL 3000; POLYVINYL ALCOHOL, UNSPECIFIED; TALC; TITANIUM DIOXIDE

SPL UNCLASSIFIED SECTION

Rx Only

To reduce the development of drug-resistant bacteria and maintain the effectiveness of clarithromycin extended-release tablets and other antibacterial drugs, clarithromycin tablets should be used only to treat or prevent infections that are proven or strongly suspected to be caused by bacteria.

DESCRIPTION

Clarithromycin is a semi-synthetic macrolide antibiotic. Chemically, it is 6- 0 -methylerythromycin. The molecular formula is C38H69NO13, and the molecular weight is 747.96. The structural formula is:

[Clarithromycin structural formula]

Clarithromycin is a white to off-white crystalline powder. It is soluble in acetone, slightly soluble in methanol, ethanol, and acetonitrile, and practically insoluble in water.

Each yellow oval film-coated clarithromycin extended-release tablet, for oral administration, contains 500 mg of clarithromycin and the following inactive ingredients: compressible sugar, D&C yellow #10 Lake, glycerol monostearate, polyethylene glycol 3000, polyvinyl alcohol, sodium phosphate monobasic (anhydrous), talc and titanium dioxide.

Meets USP requirements for dissolution test 2.

CLINICAL PHARMACOLOGY

Pharmacokinetics

Clarithromycin is rapidly absorbed from the gastrointestinal tract after oral administration. The absolute bioavailability of 250 mg clarithromycin tablets was approximately 50%. For a single 500 mg dose of clarithromycin, food slightly delays the onset of clarithromycin absorption, increasing the peak time from approximately 2 to 2.5 hours. Food also increases the clarithromycin peak plasma concentration by about 24%, but does not affect the extent of clarithromycin bioavailability. Food does not affect the onset of formation of the antimicrobially active metabolite, 14-OH clarithromycin or its peak plasma concentration but does slightly decrease the extent of metabolite formation, indicated by an 11% decrease in area under the plasma concentration-time curve (AUC). Therefore, clarithromycin tablets may be given without regard to food.

In nonfasting healthy human subjects (males and females), peak plasma concentrations were attained within 2 to 3 hours after oral dosing. Steady-state peak plasma clarithromycin concentrations were attained within 3 days and were approximately 1 to 2 mcg/mL with a 250 mg dose administered every 12 hours and 3 to 4 mcg/mL with a 500 mg dose administered every 8 to 12 hours. The elimination half-life of clarithromycin was about 3 to 4 hours with 250 mg administered every 12 hours but increased to 5 to 7 hours with 500 mg administered every 8 to 12 hours. The nonlinearity of clarithromycin pharmacokinetics is slight at the recommended doses of 250 mg and 500 mg administered every 8 to 12 hours. With a 250 mg every 12 hours dosing, the principal metabolite, 14-OH clarithromycin, attains a peak steady-state concentration of about 0.6 mcg/mL and has an elimination half-life of 5 to 6 hours. With a 500 mg every 8 to 12 hours dosing, the peak steady-state concentration of 14-OH clarithromycin is slightly higher (up to 1 mcg/mL), and its elimination half-life is about 7 to 9 hours. With any of these dosing regimens, the steady-state concentration of this metabolite is generally attained within 3 to 4 days.

After a 250 mg tablet every 12 hours, approximately 20% of the dose is excreted in the urine as clarithromycin, while after a 500 mg tablet every 12 hours, the urinary excretion of clarithromycin is somewhat greater, approximately 30%. In comparison, after an oral dose of 250 mg (125 mg/5 mL) suspension every 12 hours, approximately 40% is excreted in urine as clarithromycin. The renal clearance of clarithromycin is, however, relatively independent of the dose size and approximates the normal glomerular filtration rate. The major metabolite found in urine is 14-OH clarithromycin, which accounts for an additional 10% to 15% of the dose with either a 250 mg or a 500 mg tablet administered every 12 hours.

Steady-state concentrations of clarithromycin and 14-OH clarithromycin observed following administration of 500 mg doses of clarithromycin every 12 hours to adult patients with HIV infection were similar to those observed in healthy volunteers. In adult HIV-infected patients taking 500 or 1000 mg doses of clarithromycin every 12 hours, steady-state clarithromycin Cmax values ranged from 2 to 4 mcg/mL and 5 to 10 mcg/mL, respectively.

The steady-state concentrations of clarithromycin in subjects with impaired hepatic function did not differ from those in normal subjects; however, the 14-OH clarithromycin concentrations were lower in the hepatically impaired subjects. The decreased formation of 14-OH clarithromycin was at least partially offset by an increase in renal clearance of clarithromycin in the subjects with impaired hepatic function when compared to healthy subjects.

The pharmacokinetics of clarithromycin was also altered in subjects with impaired renal function (see PRECAUTIONS and DOSAGE AND ADMINISTRATION).

Clarithromycin and the 14-OH clarithromycin metabolite distribute readily into body tissues and fluids. There are no data available on cerebrospinal fluid penetration. Because of high intracellular concentrations, tissue concentrations are higher than serum concentrations. Examples of tissue and serum concentrations are presented below.

CONCENTRATION (after 250 mg q12h)
Tissue Type Tissue
(mcg/g) Serum
(mcg/mL)
Tonsil 1.6 0.8
Lung 8.8 1.7

Clarithromycin extended-release tablets provide extended absorption of clarithromycin from the gastrointestinal tract after oral administration. Relative to an equal total daily dose of immediate-release clarithromycin tablets, clarithromycin extended-release tablets provide lower and later steady-state peak plasma concentrations but equivalent 24-hour AUC's for both clarithromycin and its microbiologically-active metabolite, 14-OH clarithromycin. While the extent of formation of 14-OH clarithromycin following administration of clarithromycin extended-release tablets (2 × 500 mg once daily) is not affected by food, administration under fasting conditions is associated with approximately 30% lower clarithromycin AUC relative to administration with food. Therefore, clarithromycin extended-release tablets should be taken with food.

[Steady-State Clarithromycin Plasma Concentration-Time Profiles]

Steady-State Clarithromycin Plasma Concentration-Time Profiles

In healthy human subjects, steady-state peak plasma clarithromycin concentrations of approximately 2 to 3 mcg/mL were achieved about 5 to 8 hours after oral administration of 2 x 500 mg clarithromycin extended-release tablets once daily; for 14-OH clarithromycin, steady-state peak plasma concentrations of approximately 0.8 mcg/mL were attained about 6 to 9 hours after dosing. Steady-state peak plasma clarithromycin concentrations of approximately 1 to 2 mcg/mL were achieved about 5 to 6 hours after oral administration of a single 500 mg clarithromycin extended-release tablet once daily; for 14-OH clarithromycin, steady-state peak plasma concentrations of approximately 0.6 mcg/mL were attained about 6 hours after dosing.

Microbiology

Clarithromycin exerts its antibacterial action by binding to the 50S ribosomal subunit of susceptible bacteria resulting in inhibition of protein synthesis.

Clarithromycin is active in vitro against a variety of aerobic and anaerobic Gram-positive and Gram-negative bacteria as well as most Mycobacterium avium complex (MAC) bacteria.

Additionally, the 14-OH clarithromycin metabolite also has clinically significant antimicrobial activity. The 14-OH clarithromycin is twice as active against Haemophilus influenzae microorganisms as the parent compound. However, for Mycobacterium avium complex (MAC) isolates the 14-OH metabolite is 4 to 7 times less active than clarithromycin. The clinical significance of this activity against Mycobacterium avium complex is unknown.

Clarithromycin has been shown to be active against most strains of the following microorganisms both in vitro and in clinical infections as described in the INDICATIONS AND USAGE section:

Gram-Positive Microorganisms
Staphylococcus aureus
Streptococcus pneumoniae
Streptococcus pyogenes

Gram-Negative Microorganisms
Haemophilus influenzae
Haemophilus parainfluenzae
Moraxella catarrhalis

Other Microorganisms
Mycoplasma pneumoniae
Chlamydophila pneumoniae (TWAR) [previously Chlamydia pneumoniae]

The following in vitro data are available, but their clinical significance is unknown. Clarithromycin exhibits in vitro activity against most isolates of the following bacteria; however, the safety and effectiveness of clarithromycin in treating clinical infections due to these bacteria have not been established in adequate and well-controlled clinical trials.

Gram-Positive Bacteria
Streptococcus agalactiae
Streptococci (Groups C, F, G)
Viridans group streptococci

Gram-Negative Bacteria
Bordetella pertussis
Legionella pneumophila
Pasteurella multocida

Gram-Positive Bacteria
Clostridium perfringens
Peptococcus niger
Propionibacterium acnes

Gram-Negative Anaerobic Bacteria
Prevotella melaninogenica (formerly Bacteriodes melaninogenicus)

Susceptibility Testing Methods

Dilution Techniques

Quantitative methods are used to determine antimicrobial minimum inhibitory concentrations (MICs). These MICs provide estimates of the susceptibility of bacteria to antimicrobial compounds. The MICs should be determined using a standardized procedure. Standardized procedures are based on a dilution method1 (broth or agar) or equivalent with standardized inoculum concentrations and standardized concentrations of clarithromycin powder. The MIC values should be interpreted according to the following criteria2:

Susceptibility Test Interpretive Criteria for Staphylococcus aureus
MIC (mcg/mL) Interpretation
≤ 2.0 Susceptible (S)
4.0 Intermediate (I)
≥ 8.0 Resistant (R)

Susceptibility Test Interpretive Criteria for Streptococcus pyogenes and Streptococcus pneumoniaa
a These interpretive standards are applicable only to broth microdilution susceptibility tests using cation-adjusted Mueller-Hinton broth with 2-5% lysed horse blood.
MIC (mcg/mL) Interpretation
≤ 0.25 Susceptible (S)
0.5 Intermediate (I)
≥ 1.0 Resistant (R)

For testing Haemophilusspp.b
b These interpretive standards are applicable only to broth microdilution susceptibility tests with Haemophilus spp. using Haemophilus Testing Medium (HTM).1
Note: When testing Streptococcus pyogenes and Streptococcus pneumoniae, susceptibility and resistance to clarithromycin can be predicted using erythromycin.
MIC (mcg/mL) Interpretation
≤ 8.0 Susceptible (S)
16.0 Intermediate (I)
≥ 32.0 Resistant (R)

A report of "Susceptible" indicates that the pathogen is likely to be inhibited if the antimicrobial compound in the blood reaches the concentrations usually achievable. A report of "Intermediate" indicates that the result should be considered equivocal, and, if the microorganism is not fully susceptible to alternative, clinically feasible drugs, the test should be repeated. This category implies possible clinical applicability in body sites where the drug is physiologically concentrated or in situations where high dosage of drug can be used. This category also provides a buffer zone which prevents small uncontrolled technical factors from causing major discrepancies in interpretation. A report of "Resistant" indicates that the pathogen is not likely to be inhibited if the antimicrobial compound in the blood reaches the concentrations usually achievable; other therapy should be selected.

Quality Control

Standardized susceptibility test procedures require the use of laboratory control bacteria to monitor and ensure the accuracy and precision of supplies and reagents in the assay, and the techniques of the individual performing the test.1,2 Standard clarithromycin powder should provide the following MIC ranges.

cATCC is a registered trademark of the American Type Culture Collection.
d This quality control range is applicable only to S. pneumoniae ATCC 49619 tested by a microdilution procedure using cation-adjusted Mueller-Hinton broth with 2-5% lysed horse blood.
e This quality control range is applicable only to H. influenzae ATCC 49247 tested by a microdilution procedure using HTM1.

QC Strain MIC (mcg/mL)
S. aureus ATCC® 29213c 0.12 to 0.5
S. pneumoniaed ATCC 49619 0.03 to 0.12
Haemophilus influenzaee ATCC 49247 4 to 16

Diffusion Techniques

Quantitative methods that require measurement of zone diameters also provide reproducible estimates of the susceptibility of bacteria to antimicrobial compounds. The zone size provides an estimate of the susceptibility of bacteria to antimicrobial compounds. The zone size should be determined using a standardized method.2,3 The procedure uses paper disks impregnated with 15 mcg of clarithromycin to test the susceptibility of bacteria. The disk diffusion interpretive criteria are provided below.

Susceptibility Test Interpretive Criteria for Staphylococcus aureus
Zone diameter (mm) Interpretation
≥ 18 Susceptible (S)
14 to 17 Intermediate (I)
≤ 13 Resistant (R)

Susceptibility Test Interpretive Criteria for Streptococcus pyogenes and Streptococcus pneumoniae f
f These zone diameter standards only apply to tests performed using Mueller-Hinton agar supplemented with 5% sheep blood incubated in 5% CO2.
Zone diameter (mm) Interpretation
≥ 21 Susceptible (S)
17 to 20 Intermediate (I)
≤ 16 Resistant (R)

For testing Haemophilus spp. g
g These zone diameter standards are applicable only to tests with Haemophilus spp. using HTM2.
Note: When testing Streptococcus pyogenes and Streptococcus pneumoniae, susceptibility and resistance to clarithromycin can be predicted using erythromycin.
Zone diameter (mm) Interpretation
≥ 13 Susceptible (S)
11 to 12 Intermediate (I)
≤ 10 Resistant (R)

Quality Control

Standardized susceptibility test procedures require the use of laboratory control bacteria to monitor and ensure the accuracy and precision of supplies and reagents in the assay, and the techniques of the individual performing the test.2,3 For the diffusion technique using the 15 mcg disk, the criteria in the following table should be achieved.

Acceptable Quality Control Ranges for Clarithromycin
h This quality control range is applicable only to tests performed by disk diffusion using Mueller-Hinton agar supplemented with 5% defibrinated sheep blood.
i This quality control limit applies to tests conducted with Haemophilus influenzae ATCC 49247 using HTM2.

INDICATIONS AND USAGE

Adults (Clarithromycin Extended-Release Tablets, USP)

Clarithromycin extended-release tablets, USP are indicated for the treatment of adults with mild to moderate infection caused by susceptible strains of the designated microorganisms in the conditions listed below:

Acute maxillary sinusitis due to Haemophilus influenzae, Moraxella catarrhalis, or Streptococcus pneumoniae.

Acute bacterial exacerbation of chronic bronchitis due to Haemophilus influenzae, Haemophilus parainfluenzae, Moraxella catarrhalis, or Streptococcus pneumoniae.

Community-Acquired Pneumonia due to Haemophilus influenzae, Haemophilus parainfluenzae, Moraxella catarrhalis, Streptococcus pneumoniae, Chlamydophila pneumoniae (TWAR), or Mycoplasma pneumoniae.

THE EFFICACY AND SAFETY OF CLARITHROMYCIN EXTENDED-RELEASE TABLETS, USP IN TREATING OTHER INFECTIONS FOR WHICH OTHER FORMULATIONS OF CLARITHROMYCIN ARE APPROVED HAVE NOT BEEN ESTABLISHED.
To reduce the development of drug-resistant bacteria and maintain the effectiveness of clarithromycin extended-release tablets, USP and other antibacterial drugs, clarithromycin extended-release tablets, USP should be used only to treat or prevent infections that are proven or strongly suspected to be caused by susceptible bacteria. When culture and susceptibility information are available, they should be considered in selecting or modifying antibacterial therapy. In the absence of such data, local epidemiology and susceptibility patterns may contribute to the empiric selection of therapy.

CONTRAINDICATIONS

Clarithromycin is contraindicated in patients with a known hypersensitivity to clarithromycin or any of its excipients, erythromycin, or any of the macrolide antibiotics.

Clarithromycin is contraindicated in patients with a history of cholestatic jaundice/hepatic dysfunction associated with prior use of clarithromycin.

Concomitant administration of clarithromycin and any of the following drugs is contraindicated: cisapride, pimozide, astemizole, terfenadine, and ergotamine or dihydroergotamine (see DRUG INTERACTIONS). There have been postmarketing reports of drug interactions when clarithromycin and/or erythromycin are coadministered with cisapride, pimozide, astemizole, or terfenadine resulting in cardiac arrhythmias (QT prolongation, ventricular tachycardia, ventricular fibrillation, and torsades de pointes) most likely due to inhibition of metabolism of these drugs by erythromycin and clarithromycin. Fatalities have been reported.

Concomitant administration of clarithromycin and colchicine is contraindicated in patients with renal or hepatic impairment.

Clarithromycin should not be given to patients with history of QT prolongation or ventricular cardiac arrhythmia, including torsades de pointes.

Clarithromycin should not be used concomitantly with HMG-CoA reductase inhibitors (statins) that are extensively metabolized by CYP3A4 (lovastatin or simvastatin), due to the increased risk of myopathy, including rhabdomyolysis. (see WARNINGS).

For information about contraindications of other drugs indicated in combination with clarithromycin, refer to the CONTRAINDICATIONS section of their package inserts.

WARNINGS

Use In Pregnancy

CLARITHROMYCIN SHOULD NOT BE USED IN PREGNANT WOMEN EXCEPT IN CLINICAL CIRCUMSTANCES WHERE NO ALTERNATIVE THERAPY IS APPROPRIATE. IF PREGNANCY OCCURS WHILE TAKING THIS DRUG, THE PATIENT SHOULD BE APPRISED OF THE POTENTIAL HAZARD TO THE FETUS. CLARITHROMYCIN HAS DEMONSTRATED ADVERSE EFFECTS OF PREGNANCY OUTCOME AND/OR EMBRYO-FETAL DEVELOPMENT IN MONKEYS, RATS, MICE, AND RABBITS AT DOSES THAT PRODUCED PLASMA LEVELS 2 TO 17 TIMES THE SERUM LEVELS ACHIEVED IN HUMANS TREATED AT THE MAXIMUM RECOMMENDED HUMAN DOSES (see PRECAUTIONS - PREGNANCY).

Hepatotoxicity

Hepatic dysfunction, including increased liver enzymes, and hepatocellular and/or cholestatic hepatitis, with or without jaundice, has been reported with clarithromycin. This hepatic dysfunction may be severe and is usually reversible. In some instances, hepatic failure with fatal outcome has been reported and generally has been associated with serious underlying diseases and/or concomitant medications. Symptoms of hepatitis can include anorexia, jaundice, dark urine, pruritus, or tender abdomen. Discontinue clarithromycin immediately if signs and symptoms of hepatitis occur.

QT Prolongation

Clarithromycin has been associated with prolongation of the QT interval and infrequent cases of arrhythmia. Cases of torsades de pointes have been spontaneously reported during postmarketing surveillance in patients receiving clarithromycin. Fatalities have been reported. Clarithromycin should be avoided in patients with ongoing proarrhythmic conditions such as uncorrected hypokalemia or hypomagnesemia, clinically significant bradycardia (see CONTRAINDICATIONS) and in patients receiving Class IA (quinidine, procainamide) or Class III (dofetilide, amiodarone, sotalol) antiarrhythmic agents. Elderly patients may be more susceptible to drug-associated effects on the QT interval.

Drug Interactions

Serious adverse reactions have been reported in patients taking clarithromycin concomitantly with CYP3A4 substrates. These include colchicine toxicity with colchicine; rhabdomyolysis with simvastatin, lovastatin, and atorvastatin; hypoglycemia with disopyramide; and hypotension and acute kidney injury with calcium channel blockers metabolized by CYP3A4 (e.g., verapamil, amlodipine, diltiazem, nifedipine). Most reports of acute kidney injury with calcium channel blockers metabolized by CYP3A4 involved elderly patients 65 years of age or older (see CONTRAINDICATIONS and PRECAUTIONS - DRUG INTERACTIONS). Clarithromycin should be used with caution when administered concurrently with medications that induce the cytochrome CYP3A4 enzyme (see PRECAUTIONS - DRUG INTERACTIONS).

Colchicine

Life-threatening and fatal drug interactions have been reported in patients treated with clarithromycin and colchicine. Clarithromycin is a strong CYP3A4 inhibitor and this interaction may occur while using both drugs at their recommended doses. If coadministration of clarithromycin and colchicine is necessary in patients with normal renal and hepatic function, the dose of colchicine should be reduced. Patients should be monitored for clinical symptoms of colchicine toxicity. Concomitant administration of clarithromycin and colchicine is contraindicated in patients with renal or hepatic impairment (see CONTRAINDICATIONS and PRECAUTIONS – DRUG INTERACTIONS).
Benzodiazepines

Increased sedation and prolongation of sedation have been reported with concomitant administration of clarithromycin and triazolobenzodiazepines, such as triazolam, and midazolam.

Quetiapine

Use quetiapine and clarithromycin concomitantly with caution. Coadministration could result in increased quetiapine exposure and quetiapine related toxicities such as somnolence, orthostatic hypotension, altered state of consciousness, neuroleptic malignant syndrome, and QT prolongation. Refer to quetiapine prescribing information for recommendations on dose reduction if coadministered with CYP3A4 inhibitors such as clarithromycin.

Oral Hypoglycemic Agents/Insulin

The concomitant use of clarithromycin and oral hypoglycemic agents and/or insulin can result in significant hypoglycemia. With certain hypoglycemic drugs such as nateglinide, pioglitazone, repaglinide and rosiglitazone, inhibition of CYP3A enzyme by clarithromycin may be involved and could cause hypoglycemia when used concomitantly. Careful monitoring of glucose is recommended.

Oral Anticoagulants

There is a risk of serious hemorrhage and significant elevations in INR and prothrombin time when clarithromycin is coadministered with warfarin. INR and prothrombin times should be frequently monitored while patients are receiving clarithromycin and oral anticoagulants concurrently.

HMG-CoA Reductase Inhibitors (statins)

Concomitant use of clarithromycin with lovastatin or simvastatin is contraindicated (see CONTRAINDICATIONS) as these statins are extensively metabolized by CYP3A4, and concomitant treatment with clarithromycin increases their plasma concentration, which increases the risk of myopathy, including rhabdomyolysis. Cases of rhabdomyolysis have been reported in patients taking clarithromycin concomitantly with these statins. If treatment with clarithromycin cannot be avoided, therapy with lovastatin or simvastatin must be suspended during the course of treatment.

Caution should be exercised when prescribing clarithromycin with statins. In situations where the concomitant use of clarithromycin with atorvastatin or pravastatin cannot be avoided, atorvastatin dose should not exceed 20 mg daily and pravastatin dose should not exceed 40 mg daily. Use of a statin that is not dependent on CYP3A metabolism (e.g. fluvastatin) can be considered. It is recommended to prescribe the lowest registered dose if concomitant use cannot be avoided.

Clostridium difficile Associated Diarrhea

Clostridium difficile associated diarrhea (CDAD) has been reported with use of nearly all antibacterial agents, including clarithromycin extended-release tablets, and may range in severity from mild diarrhea to fatal colitis. Treatment with antibacterial agents alters the normal flora of the colon leading to overgrowth of C. difficile.

C. difficile produces toxins A and B which contribute to the development of CDAD. Hypertoxin producing strains of C. difficile cause increased morbidity and mortality, as these infections can be refractory to antimicrobial therapy and may require colectomy. CDAD must be considered in all patients who present with diarrhea following antibiotic use. Careful medical history is necessary since CDAD has been reported to occur over two months after the administration of antibacterial agents.

If CDAD is suspected or confirmed, ongoing antibiotic use not directed against C. difficile may need to be discontinued. Appropriate fluid and electrolyte management, protein supplementation, antibiotic treatment of C. difficile, and surgical evaluation should be instituted as clinically indicated.

Acute Hypersensitivity Reactions

In the event of severe acute hypersensitivity reactions, such as anaphylaxis, Stevens-Johnson Syndrome, toxic epidermal necrolysis, drug rash with eosinophilia and systemic symptoms (DRESS), and Henoch-Schonlein purpura clarithromycin therapy should be discontinued immediately and appropriate treatment should be urgently initiated.

Combination Therapy with Other Drugs

For information about warnings of other drugs indicated in combination with clarithromycin, refer to the WARNINGS section of their package inserts.

PRECAUTIONS

General

Prescribing clarithromycin extended-release tablets in the absence of a proven or strongly suspected bacterial infection or a prophylactic indication is unlikely to provide benefit to the patient and increases the risk of the development of drug-resistant bacteria.

Clarithromycin is principally excreted via the liver and kidney.

Clarithromycin may be administered without dosage adjustment to patients with hepatic impairment and normal renal function. However, in the presence of severe renal impairment with or without coexisting hepatic impairment, decreased dosage or prolonged dosing intervals may be appropriate.

Exacerbation of symptoms of myasthenia gravis and new onset of symptoms of myasthenic syndrome has been reported in patients receiving clarithromycin therapy.

Information to Patients

Patients should be counseled that antibacterial drugs including clarithromycin extended-release tablets should only be used to treat bacterial infections. They do not treat viral infections (e.g., the common cold). When clarithromycin extended-release tablets are prescribed to treat a bacterial infection, patients should be told that although it is common to feel better early in the course of therapy, the medication should be taken exactly as directed. Skipping doses or not completing the full course of therapy may (1) decrease the effectiveness of the immediate treatment and (2) increase the likelihood that bacteria will develop resistance and will not be treatable by clarithromycin extended-release tablets or other antibacterial drugs in the future.

Diarrhea is a common problem caused by antibiotics which usually ends when the antibiotic is discontinued. Sometimes after starting treatment with antibiotics, patients can develop watery and bloody stools (with or without stomach cramps and fever) even as late as two or more months after having taken the last dose of the antibiotic. If this occurs, patients should contact their physician as soon as possible.

Clarithromycin may interact with some drugs; therefore patients should be advised to report to their doctor the use of any other medications. Clarithromycin extended-release tablets should be taken with food.

Drug Interactions

Clarithromycin use in patients who are receiving theophylline may be associated with an increase of serum theophylline concentrations. Monitoring of serum theophylline concentrations should be considered for patients receiving high doses of theophylline or with baseline concentrations in the upper therapeutic range. In two studies in which theophylline was administered with clarithromycin (a theophylline sustained-release formulation was dosed at either 6.5 mg/kg or 12 mg/kg together with 250 or 500 mg q12h clarithromycin), the steady-state levels of Cmax, Cmin, and the area under the serum concentration time curve (AUC) of theophylline increased about 20%.

Hypotension, bradyarrhythmias, and lactic acidosis have been observed in patients receiving concurrent verapamil, belonging to the calcium channel blockers drug class.

Concomitant administration of single doses of clarithromycin and carbamazepine has been shown to result in increased plasma concentrations of carbamazepine. Blood level monitoring of carbamazepine may be considered.

When clarithromycin and terfenadine were coadministered, plasma concentrations of the active acid metabolite of terfenadine were threefold higher, on average, than the values observed when terfenadine was administered alone. The pharmacokinetics of clarithromycin and the 14-OH-clarithromycin were not significantly affected by coadministration of terfenadine once clarithromycin reached steady-state conditions. Concomitant administration of clarithromycin with terfenadine is contraindicated (see CONTRAINDICATIONS).

Simultaneous oral administration of clarithromycin tablets and zidovudine to HIV-infected adult patients may result in decreased steady-state zidovudine concentrations. Following administration of clarithromycin 500 mg tablets twice daily with zidovudine 100 mg every 4 hours, the steady-state zidovudine AUC decreased 12% compared to administration of zidovudine alone (n=4). Individual values ranged from a decrease of 34% to an increase of 14%. When clarithromycin tablets were administered two to four hours prior to zidovudine, the steady-state zidovudine Cmax increased 100% whereas the AUC was unaffected (n=24). Administration of clarithromycin and zidovudine should be separated by at least two hours. The impact of coadministration of clarithromycin extended-release tablets and zidovudine has not been evaluated.

Simultaneous administration of clarithromycin tablets and didanosine to 12 HIV-infected adult patients resulted in no statistically significant change in didanosine pharmacokinetics.

Following administration of fluconazole 200 mg daily and clarithromycin 500 mg twice daily to 21 healthy volunteers, the steady-state clarithromycin Cmin and AUC increased 33% and 18%, respectively. Steady-state concentrations of 14-OH clarithromycin were not significantly affected by concomitant administration of fluconazole. No dosage adjustment of clarithromycin is necessary when coadministered with fluconazole.

Ritonavir

Concomitant administration of clarithromycin and ritonavir (n=22) resulted in a 77% increase in clarithromycin AUC and a 100% decrease in the AUC of 14-OH clarithromycin. Clarithromycin may be administered without dosage adjustment to patients with normal renal function taking ritonavir. Since concentrations of 14-OH clarithromycin are significantly reduced when clarithromycin is coadministered with ritonavir, alternative antibacterial therapy should be considered for indications other than infections due to Mycobacterium avium complex (see PRECAUTIONS – DRUG INTERACTIONS). Doses of clarithromycin greater than 1000 mg per day should not be coadministered with protease inhibitors.

Spontaneous reports in the postmarketing period suggest that concomitant administration of clarithromycin and oral anticoagulants may potentiate the effects of the oral anticoagulants. Prothrombin times should be carefully monitored while patients are receiving clarithromycin and oral anticoagulants simultaneously.

Digoxin is a substrate for P-glycoprotein (Pgp) and clarithromycin is known to inhibit Pgp. When clarithromycin and digoxin are coadministered, inhibition of Pgp by clarithromycin may lead to increased exposure of digoxin. Elevated digoxin serum concentrations in patients receiving clarithromycin and digoxin concomitantly have been reported in postmarketing surveillance. Some patients have shown clinical signs consistent with digoxin toxicity, including potentially fatal arrhythmias. Monitoring of serum digoxin concentrations should be considered, especially for patients with digoxin concentrations in the upper therapeutic range.

Coadministration of clarithromycin, known to inhibit CYP3A, and a drug primarily metabolized by CYP3A may be associated with elevations in drug concentrations that could increase or prolong both therapeutic and adverse effects of the concomitant drug.

Clarithromycin should be used with caution in patients receiving treatment with other drugs known to be CYP3A enzyme substrates, especially if the CYP3A substrate has a narrow safety margin (e.g., carbamazepine) and/or the substrate is extensively metabolized by this enzyme. Dosage adjustments may be considered, and when possible, serum concentrations of drugs primarily metabolized by CYP3A should be monitored closely in patients concurrently receiving clarithromycin.

The following are examples of some clinically significant CYP3A based drug interactions. Interactions with other drugs metabolized by the CYP3A isoform are also possible.

Carbamazepine and Terfenadine

Increased serum concentrations of carbamazepine and the active acid metabolite of terfenadine were observed in clinical trials with clarithromycin.

Colchicine

Colchicine is a substrate for both CYP3A and the efflux transporter, P-glycoprotein (Pgp). Clarithromycin and other macrolides are known to inhibit CYP3A and Pgp. When a single dose of colchicine 0.6 mg was administered with clarithromycin 250 mg BID for 7 days, the colchicine Cmax increased 197% and the AUC0-∞ increased 239% compared to administration of colchicine alone. The dose of colchicine should be reduced when coadministered with clarithromycin in patients with normal renal and hepatic function. Concomitant use of clarithromycin and colchicine is contraindicated in patients with renal or hepatic impairment (see WARNINGS).

Efavirenz, Nevirapine, Rifampicin, Rifabutin, and Rifapentine

Inducers of CYP3A enzymes, such as efavirenz, nevirapine, rifampicin, rifabutin, and rifapentine will increase the metabolism of clarithromycin, thus decreasing plasma concentrations of clarithromycin, while increasing those of 14-OH-clarithromycin. Since the microbiological activities of clarithromycin and 14-OH-clarithromycin are different for different bacteria, the intended therapeutic effect could be impaired during concomitant administration of clarithromycin and enzyme inducers. Alternative antibacterial treatment should be considered when treating patients receiving inducers of CYP3A. Concomitant administration of rifabutin and clarithromycin resulted in an increase in rifabutin, and decrease in clarithromycin serum levels together with an increased risk of uveitis.

Etravirine

Clarithromycin exposure was decreased by etravirine; however, concentrations of the active metabolite, 14-OH-clarithromycin, were increased. Because 14-OH-clarithromycin has reduced activity against Mycobacterium avium complex (MAC), overall activity against this pathogen may be altered; therefore alternatives to clarithromycin should be considered for the treatment of MAC.

Sildenafil, Tadalafil, and Vardenafil

Each of these phosphodiesterase inhibitors is primarily metabolized by CYP3A, and CYP3A will be inhibited by concomitant administration of clarithromycin. Coadministration of clarithromycin with sildenafil, tadalafil, or vardenafil will result in increased exposure of these phosphodiesterase inhibitors. Coadministration of these phosphodiesterase inhibitors with clarithromycin is not recommended.

Tolterodine

The primary route of metabolism for tolterodine is via CYP2D6. However, in a subset of the population devoid of CYP2D6, the identified pathway of metabolism is via CYP3A. In this population subset, inhibition of CYP3A results in significantly higher serum concentrations of tolterodine. Tolterodine 1 mg twice daily is recommended in patients deficient in CYP2D6 activity (poor metabolizers) when coadministered with clarithromycin.

Triazolobenzodiazepines (e.g., alprazolam, midazolam, triazolam)

When a single dose of midazolam was coadministered with clarithromycin tablets (500 mg twice daily for 7 days), midazolam AUC increased 174% after intravenous administration of midazolam and 600% after oral administration. When oral midazolam is coadministered with clarithromycin, dose adjustments may be necessary and possible prolongation and intensity of effect should be anticipated. Caution and appropriate dose adjustments should be considered when triazolam or alprazolam is coadministered with clarithromycin. For benzodiazepines which are not metabolized by CYP3A (e.g., temazepam, nitrazepam, lorazepam), a clinically important interaction with clarithromycin is unlikely.

There have been postmarketing reports of drug interactions and central nervous system (CNS) effects (e.g., somnolence and confusion) with the concomitant use of clarithromycin and triazolam. Monitoring the patient for increased CNS pharmacological effects is suggested.

Atazanavir

Both clarithromycin and atazanavir are substrates and inhibitors of CYP3A, and there is evidence of a bi-directional drug interaction. Following administration of clarithromycin (500 mg twice daily) with atazanavir (400 mg once daily), the clarithromycin AUC increased 94%, the 14-OH clarithromycin AUC decreased 70% and the atazanavir AUC increased 28%. When clarithromycin is coadministered with atazanavir, the dose of clarithromycin should be decreased by 50%. Since concentrations of 14-OH clarithromycin are significantly reduced when clarithromycin is coadministered with atazanavir, alternative antibacterial therapy should be considered for indications other than infections due to Mycobacterium avium complex (see PRECAUTIONS – DRUG INTERACTIONS). Doses of clarithromycin greater than 1000 mg per day should not be coadministered with protease inhibitors.

Itraconazole

Both clarithromycin and itraconazole are substrates and inhibitors of CYP3A, potentially leading to a bi-directional drug interaction when administered concomitantly. Clarithromycin may increase the plasma concentrations of itraconazole, while itraconazole may increase the plasma concentrations of clarithromycin. Patients taking itraconazole and clarithromycin concomitantly should be monitored closely for signs or symptoms of increased or prolonged adverse reactions.

Saquinavir

Both clarithromycin and saquinavir are substrates and inhibitors of CYP3A and there is evidence of a bi-directional drug interaction. Following administration of clarithromycin (500 mg bid) and saquinavir (soft gelatin capsules, 1200 mg tid) to 12 healthy volunteers, the steady-state saquinavir AUC and Cmaxincreased 177% and 187% respectively compared to administration of saquinavir alone. Clarithromycin AUC and Cmax increased 45% and 39% respectively, whereas the 14–OH clarithromycin AUC and Cmaxdecreased 24% and 34% respectively, compared to administration with clarithromycin alone. No dose adjustment of clarithromycin is necessary when clarithromycin is coadministered with saquinavir in patients with normal renal function. When saquinavir is coadministered with ritonavir, consideration should be given to the potential effects of ritonavir on clarithromycin (refer to interaction between clarithromycin and ritonavir) (see PRECAUTIONS – DRUG INTERACTIONS).

The following CYP3A based drug interactions have been observed with erythromycin products and/or with clarithromycin in postmarketing experience:

Antiarrhythmics
There have been postmarketing reports of torsades de pointes occurring with concurrent use of clarithromycin and quinidine or disopyramide. Electrocardiograms should be monitored for QTc prolongation during coadministration of clarithromycin with these drugs. Serum concentrations of these medications should also be monitored.
There have been post marketing reports of hypoglycemia with the concomitant administration of clarithromycin and disopyramide. Therefore, blood glucose levels should be monitored during concomitant administration of clarithromycin and disopyramide.

Ergotamine/Dihydroergotamine
Postmarketing reports indicate that coadministration of clarithromycin with ergotamine or dihydroergotamine has been associated with acute ergot toxicity characterized by vasospasm and ischemia of the extremities and other tissues including the central nervous system. Concomitant administration of clarithromycin with ergotamine or dihydroergotamine is contraindicated (see CONTRAINDICATIONS).

Triazolobenziodidiazepines (Such as Triazolam and Alprazolam) and Related Benzodiazepines (Such as Midazolam)
Erythromycin has been reported to decrease the clearance of triazolam and midazolam, and thus, may increase the pharmacologic effect of these benzodiazepines. There have been postmarketing reports of drug interactions and CNS effects (e.g., somnolence and confusion) with the concomitant use of clarithromycin and triazolam.

Quetiapine
Quetiapine is a substrate for CYP3A4, which is inhibited by clarithromycin. Coadministration with clarithromycin could result in increased quetiapine exposure and possible quetiapine related toxicities. There have been post-marketing reports of somnolence, orthostatic hypotension, altered state of consciousness, neuroleptic malignant syndrome, and QT prolongation during concomitant administration. Refer to quetiapine prescribing information for recommendations on dose reduction if coadministered with CYP3A4 inhibitors such as clarithromycin.

Sildenafil (Viagra)
Erythromycin has been reported to increase the systemic exposure (AUC) of sildenafil. A similar interaction may occur with clarithromycin; reduction of sildenafil dosage should be considered. (See Viagra package insert.)

There have been spontaneous or published reports of CYP3A based interactions of erythromycin and/or clarithromycin with cyclosporine, carbamazepine, tacrolimus, alfentanil, disopyramide, rifabutin, quinidine, methylprednisolone, cilostazol, bromocriptine, vinblastine, phenobarbital and St. John’s Wort.

Concomitant administration of clarithromycin with cisapride, pimozide, astemizole, or terfenadine is contraindicated (see CONTRAINDICATIONS).

In addition, there have been reports of interactions of erythromycin or clarithromycin with drugs not thought to be metabolized by CYP3A, including hexobarbital, phenytoin, and valproate.

Carcinogenesis, Mutagenesis, Impairment of Fertility

The following in vitro mutagenicity tests have been conducted with clarithromycin:
Salmonella /Mammalian Microsomes Test

Bacterial Induced Mutation Frequency Test

In Vitro Chromosome Aberration Test

Rat Hepatocyte DNA Synthesis Assay

Mouse Lymphoma Assay

Mouse Dominant Lethal Study

Mouse Micronucleus Test

All tests had negative results except the In Vitro Chromosome Aberration Test which was weakly positive in one test and negative in another.

In addition, a Bacterial Reverse-Mutation Test (Ames Test) has been performed on clarithromycin metabolites with negative results.

Fertility and reproduction studies have shown that daily doses of up to 160 mg/kg/day (1.3 times the recommended maximum human dose based on mg/m2) to male and female rats caused no adverse effects on the estrous cycle, fertility, parturition, or number and viability of offspring. Plasma levels in rats after 150 mg/kg/day were 2 times the human serum levels.

In the 150 mg/kg/day monkey studies, plasma levels were 3 times the human serum levels. When given orally at 150 mg/kg/day (2.4 times the recommended maximum human dose based on mg/m2), clarithromycin was shown to produce embryonic loss in monkeys. This effect has been attributed to marked maternal toxicity of the drug at this high dose.

In rabbits, in utero fetal loss occurred at an intravenous dose of 33 mg/m2 , which is 17 times less than the maximum proposed human oral daily dose of 618 mg/m2.

Long-term studies in animals have not been performed to evaluate the carcinogenic potential of clarithromycin.

Pregnancy

Teratogenic Effects
Pregnancy Category C
Four teratogenicity studies in rats (three with oral doses and one with intravenous doses up to 160 mg/kg/day administered during the period of major organogenesis) and two in rabbits at oral doses up to 125 mg/kg/day (approximately 2 times the recommended maximum human dose based on mg/m2) or intravenous doses of 30 mg/kg/day administered during gestation days 6 to 18 failed to demonstrate any teratogenicity from clarithromycin. Two additional oral studies in a different rat strain at similar doses and similar conditions demonstrated a low incidence of cardiovascular anomalies at doses of 150 mg/kg/day administered during gestation days 6 to 15. Plasma levels after 150 mg/kg/day were 2 times the human serum levels. Four studies in mice revealed a variable incidence of cleft palate following oral doses of 1000 mg/kg/day (2 and 4 times the recommended maximum human dose based on mg/m2, respectively) during gestation days 6 to 15. Cleft palate was also seen at 500 mg/kg/day. The 1000 mg/kg/day exposure resulted in plasma levels 17 times the human serum levels. In monkeys, an oral dose of 70 mg/kg/day (an approximate equidose of the recommended maximum human dose based on mg/m2) produced fetal growth retardation at plasma levels that were 2 times the human serum levels.

There are no adequate and well-controlled studies in pregnant women. Clarithromycin should be used during pregnancy only if the potential benefit justifies the potential risk to the fetus (see WARNINGS).

Nursing Mothers

Clarithromycin and its active metabolite 14-hydroxy clarithromycin are excreted in human milk. Serum and milk samples were obtained after 3 days of treatment, at steady state, from one published study of 12 lactating women who were taking clarithromycin 250 mg orally twice daily. Based on the limited data from this study, and assuming milk consumption of 150 mL/kg/day, an exclusively human milk fed infant would receive an estimated average of 136 mcg/kg/day of clarithromycin and its active metabolite, with this maternal dosage regimen. This is less than 2% of the maternal weight-adjusted dose (7.8 mg/kg/day, based on the average maternal weight of 64 kg), and less than 1% of the pediatric dose (15 mg/kg/day) for children greater than 6 months of age.

A prospective observational study of 55 breastfed infants of mothers taking a macrolide antibiotic (6 were exposed to clarithromycin) were compared to 36 breastfed infants of mothers

taking amoxicillin. Adverse reactions were comparable in both groups. Adverse reactions occurred in 12.7% of infants exposed to macrolides and included rash, diarrhea, loss of appetite, and somnolence.

Caution should be exercised when clarithromycin is administered to nursing women. The development and health benefits of human milk feeding should be considered along with the mother’s clinical need for clarithromycin and any potential adverse effects on the human milk fed child from the drug or from the underlying maternal condition.

Pediatric Use

Safety and effectiveness of clarithromycin in pediatric patients under 6 months of age have not been established. The safety of clarithromycin has not been studied in MAC patients under the age of 20 months. Neonatal and juvenile animals tolerated clarithromycin in a manner similar to adult animals. Young animals were slightly more intolerant to acute overdosage and to subtle reductions in erythrocytes, platelets and leukocytes but were less sensitive to toxicity in the liver, kidney, thymus, and genitalia.

Geriatric Use

In a steady-state study in which healthy elderly subjects (age 65 to 81 years old) were given 500 mg every 12 hours, the maximum serum concentrations and area under the curves of clarithromycin and 14-OH clarithromycin were increased compared to those achieved in healthy young adults. These changes in pharmacokinetics parallel known age-related decreases in renal function. In clinical trials, elderly patients did not have an increased incidence of adverse events when compared to younger patients. Dosage adjustment should be considered in elderly patients with severe renal impairment. Elderly patients may be more susceptible to development of torsades de pointes arrhythmias than younger patients (see WARNINGS and PRECAUTIONS).

Most reports of acute kidney injury with calcium channel blockers metabolized by CYP3A4 (e.g., verapamil, amlodipine, diltiazem, nifedipine) involved elderly patients 65 years of age or older (see WARNINGS).

ADVERSE REACTIONS

The most frequent and common adverse reactions related to clarithromycin therapy for both adult and pediatric populations are abdominal pain, diarrhea, nausea, vomiting and dysgeusia. These adverse reactions are consistent with the known safety profile of macrolide antibiotics.

There was no significant difference in the incidence of these gastrointestinal adverse reactions during clinical trials between the patient population with or without preexisting mycobacterial infections.

Adverse Reactions Observed During Clinical Trials of Clarithromycin

The following adverse reactions were observed in clinical trials with clarithromycin at a rate greater than or equal to 1%:

Gastrointestinal Disorders
Diarrhea, vomiting, dyspepsia, nausea, abdominal pain

Hepatobiliary Disorders
Liver function test abnormal

Immune System Disorders
Anaphylactoid reaction

Infection and Infestations
Candidiasis

Nervous System Disorders
Dysgeusia, headache

Psychiatric Disorders
Insomnia

Skin and Subcutaneous Tissue Disorders
Rash

Other Adverse Reactions Observed During Clinical Trials of Clarithromycin

The following adverse reactions were observed in clinical trials with clarithromycin at a rate less than 1%:

Blood and Lymphatic System Disorders
Leukopenia, neutropenia, thrombocythemia, eosinophilia

Cardiac Disorders
Electrocardiogram QT prolonged, cardiac arrest, atrial fibrillation, extrasystoles, palpitations

Ear and Labyrinth Disorders
Vertigo, tinnitus, hearing impaired

Gastrointestinal Disorders
Stomatitis, glossitis, esophagitis, gastrooesophageal reflux disease, gastritis, proctalgia, abdominal distension, constipation, dry mouth, eructation, flatulence

General Disorders and Administration Site Conditions
Malaise, pyrexia, asthenia, chest pain, chills, fatigue

Hepatobiliary Disorders
Cholestasis, hepatitis

Immune System Disorders
Hypersensitivity

Infections and Infestations
Cellulitis, gastroenteritis, infection, vaginal infection

Investigations
Blood bilirubin increased, blood alkaline phosphatase increased, blood lactate dehydrogenase increased, albumin globulin ratio abnormal

Metabolism and Nutrition Disorders
Anorexia, decreased appetite

Musculoskeletal and Connective Tissue Disorders
Myalgia, muscle spasms, nuchal rigidity

Nervous System Disorders
Dizziness, tremor, loss of consciousness, dyskinesia, somnolence

Psychiatric Disorders
Anxiety, nervousness

Renal and Urinary Disorders
Blood creatinine increased, blood urea increased

Respiratory, Thoracic and Mediastinal Disorders
Asthma, epistaxis, pulmonary embolism

Skin and Subcutaneous Tissue Disorders
Urticaria, dermatitis bullous, pruritus, hyperhidrosis, rash maculo-papular

In the acute exacerbation of chronic bronchitis and acute maxillary sinusitis studies overall gastrointestinal adverse events were reported by a similar proportion of patients taking either clarithromycin tablets or clarithromycin extended-release tablets; however, patients taking clarithromycin extended-release tablets reported significantly less severe gastrointestinal symptoms compared to patients taking clarithromycin tablets. In addition, patients taking clarithromycin extended-release tablets had significantly fewer premature discontinuations for drug-related gastrointestinal or abnormal taste adverse events compared to clarithromycin tablets.

In community-acquired pneumonia studies conducted in adults comparing clarithromycin to erythromycin base or erythromycin stearate, there were fewer adverse events involving the digestive system in clarithromycin-treated patients compared to erythromycin-treated patients (13% vs 32%; p < 0.01). Twenty percent of erythromycin-treated patients discontinued therapy due to adverse events compared to 4% of clarithromycin-treated patients.

In two U.S. studies of acute otitis media comparing clarithromycin to amoxicillin/potassium clavulanate in pediatric patients, there were fewer adverse events involving the digestive system in clarithromycin-treated patients compared to amoxicillin/potassium clavulanate-treated patients (21% vs. 40%, p < 0.001). One-third as many clarithromycin-treated patients reported diarrhea as did amoxicillin/potassium clavulanate-treated patients.

Postmarketing Experience

The following adverse reactions have been identified during post approval use of clarithromycin. Because these reactions are reported voluntarily from a population of uncertain size, it is not always possible to reliably estimate their frequency or establish a causal relationship to drug exposure.

Blood and Lymphatic System Disorders
Thrombocytopenia, agranulocytosis

Cardiac Disorders
Torsades de pointes, ventricular tachycardia, ventricular arrhythmia

Ear and Labyrinth Disorders
Deafness was reported chiefly in elderly women and was usually reversible.

Gastrointestinal Disorders
Pancreatitis acute, tongue discoloration, tooth discoloration was reported and was usually reversible with professional cleaning upon discontinuation of the drug. There have been reports of clarithromycin extended-release tablets in the stool, many of which have occurred in patients with anatomic (including ileostomy or colostomy) or functional gastrointestinal disorders with shortened GI transit times. In several reports, tablet residues have occurred in the context of diarrhea. It is recommended that patients who experience tablet residue in the stool and no improvement in their condition should be switched to a different clarithromycin formulation (e.g. suspension) or another antibacterial drug.

Hepatobiliary Disorders
Hepatic failure, jaundice hepatocellular. Adverse reactions related to hepatic dysfunction have been reported with clarithromycin (see WARNINGS - HEPATOTOXICITY).

Immune System Disorders
Anaphylactic reaction, angioedema

Infections and Infestations
Pseudomembranous colitis

Investigations
Prothrombin time prolonged, white blood cell count decreased, international normalized ratio increased. Abnormal urine color has been reported, associated with hepatic failure.

Metabolism and Nutrition Disorders
Hypoglycemia has been reported in patients taking oral hypoglycemic agents or insulin.

Musculoskeletal and Connective Tissue Disorders
Myopathy, rhabdomyolysis was reported and in some of the reports, clarithromycin was administered concomitantly with statins, fibrates, colchicine or allopurinol (see CONTRAINDICATIONS and WARNINGS).

Nervous System Disorders
Convulsion, ageusia, parosmia, anosmia, paraesthesia

Psychiatric Disorders
Psychotic disorder, confusional state, depersonalization, depression, disorientation, manic behavior, hallucination, abnormal behavior, abnormal dreams. These disorders usually resolve upon discontinuation of the drug.

There are no data on the effect of clarithromycin on the ability to drive or use machines. The potential for dizziness, vertigo, confusion and disorientation, which may occur with the medication, should be taken into account before patients drive or use machines.

Renal and Urinary Disorders
Nephritis interstitial, renal failure

Skin and Subcutaneous Tissue Disorders
Stevens-Johnson syndrome, toxic epidermal necrolysis, drug rash with eosinophilia and systemic symptoms (DRESS), Henoch-Schonlein purpura, acne

Vascular Disorders
Hemorrhage

There have been reports of colchicine toxicity with concomitant use of clarithromycin and colchicine, especially in the elderly, some of which occurred in patients with renal insufficiency. Deaths have been reported in some such patients (see WARNINGS and PRECAUTIONS).

To report SUSPECTED ADVERSE EVENTS, contact Actavis at 1-800-272-5525 or FDA at 1-800-FDA-1088 or HTTP://WWW.FDA.GOV/ for voluntary reporting of adverse reactions.

OVERDOSAGE

Overdosage of clarithromycin can cause gastrointestinal symptoms such as abdominal pain, vomiting, nausea, and diarrhea.

Adverse reactions accompanying overdosage should be treated by the prompt elimination of unabsorbed drug and supportive measures. As with other macrolides, clarithromycin serum concentrations are not expected to be appreciably affected by hemodialysis or peritoneal dialysis.

DOSAGE AND ADMINISTRATION

Clarithromycin extended-release tablets should be taken with food. Clarithromycin extended-release tablets should be swallowed whole and not chewed, broken or crushed.

Clarithromycin may be administered without dosage adjustment in the presence of hepatic impairment if there is normal renal function. In patients with severe renal impairment (CLCR less than 30 mL/min), the dose of clarithromycin should be reduced by 50%. However, when patients with moderate or severe renal impairment are taking clarithromycin concomitantly with atazanavir or ritonavir, the dose of clarithromycin should be reduced by 50% or 75% for patients with CLCR of 30 to 60 mL/min or less than 30 mL/min, respectively.

ADULT DOSAGE GUIDELINES
Clarithromycin Extended-Release Tablets
Infection Dosage
(q24h) Duration
(days)
Acute maxillary sinusitis due to 2 x 500 mg 14
H.influenzae
M.catarrhalis
S. pneumoniae
Acute exacerbation of chronic bronchitis due to
H.influenzae 2 x 500 mg 7
H. parainfluenzae 2 x 500 mg 7
M. catarrhalis 2 x 500 mg 7
S. pneumoniae 2 x 500 mg 7
Community-Acquired Pneumonia due to
H.influenzae 2 x 500 mg 7
H.parainfluenzae 2 x 500 mg 7
M.catarrhalis 2 x 500 mg 7
S. pneumoniae 2 x 500 mg 7
C.pneumoniae 2 x 500 mg 7
M.pneumoniae 2 x 500 mg 7

HOW SUPPLIED

Clarithromycin extended-release tablets, USP are supplied as yellow, film coated, oval shaped tablets debossed with [Company Logo] and "777" on one side.

Bottles of 60 (NDC 0591-2805-60), bottles of 500 (NDC 0591-2805-05), bottles of 1000 (NDC 0591-2805-10).

Store clarithromycin extended-release tablets, USP at 20° to 25°C (68° to 77°F). [See USP Controlled Room Temperature.]

REFERENCES

Clinical and Laboratory Standards Institute (CLSI). Methods for Dilution Antimicrobial Susceptibility Tests for Bacteria that Grow Aerobically - 9th edition. Approved Standard. CLSI Document M07-A9, CLSI. 950 West Valley Rd, Suite 2500, Wayne, PA 19087, 2012.

CLSI. Performance Standards for Antimicrobial Susceptibility Testing, 23rd Informational Supplement, CLSI Document M100-S23, 2013.

CLSI. Performance Standards for Antimicrobial Disk Susceptibility Tests, 11th edition. Approved Standard CLSI Document M02-A11, 2012.

Manufactured by:
Actavis Laboratories FL, Inc.
Fort Lauderdale, FL 33314 USA

Distributed by:
Actavis Pharma, Inc.
Parsippany, NJ 07054 USA

Revised: January 2016